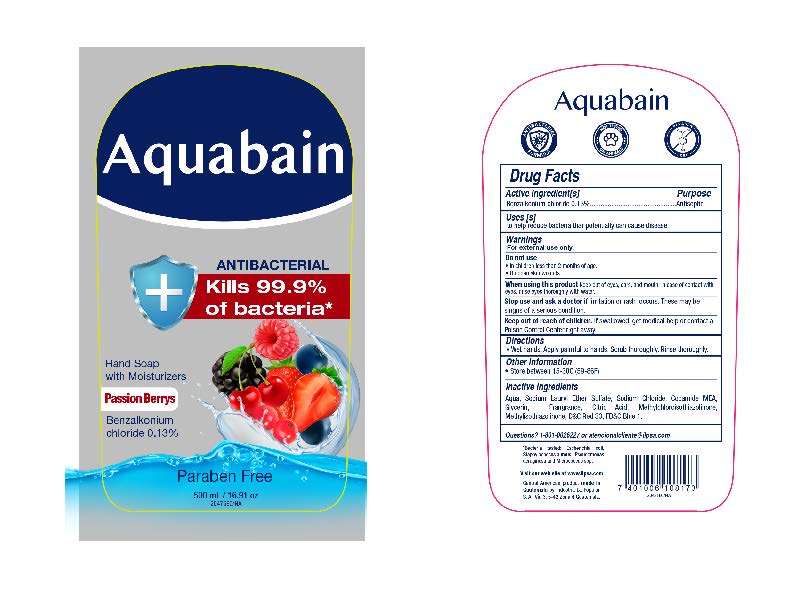 DRUG LABEL: Aquabain Antibacterial  Passion Berrys
NDC: 62476-001 | Form: LIQUID
Manufacturer: Industria La Popular, S.A.
Category: otc | Type: HUMAN OTC DRUG LABEL
Date: 20241202

ACTIVE INGREDIENTS: BENZALKONIUM CHLORIDE 0.65 g/500 mL
INACTIVE INGREDIENTS: COCAMIDE; METHYLCHLOROISOTHIAZOLINONE; SODIUM LAURYL SULFATE; WATER; GLYCERIN; METHYLISOTHIAZOLINONE; ANHYDROUS CITRIC ACID; SODIUM CHLORIDE; FD&C BLUE NO. 1; D&C RED NO. 33

Aquabain Antibacterial Hand Soap Passion Berrys

Active Ingredient

Benzalkonium Chloride 0.13%

Purpose

Antiseptic

Uses

to help reduce bacteria that potentially can cause disease.

Warnings

For External Use only.

When using this product

keep out of eyes, ears, and mouth, in case of contact with eyes, rinse eyes thoroughly with water

Stop use

if irritation or rash occurs. These may be signs of a serious condition.

Keep out of reach of children.

If swallowed, get medical help or contact a Poison Control Center right away

Directions

Wet hands. Apply palmful to hands. Scrub thoroughly. Rinse thoroughly.

Other Information

Store between 15-30C (59-86F)

Inactive Ingredients

Aqua, Sodium Lauryl Ether Sulfate, Sodium Chloride, Cocamide MEA, Glycerin, Fragrance, Citric Acid, Methylchloroisothiazolinone, Methylisothiazolinone, D&C Red 33, FD&C Blue 1.